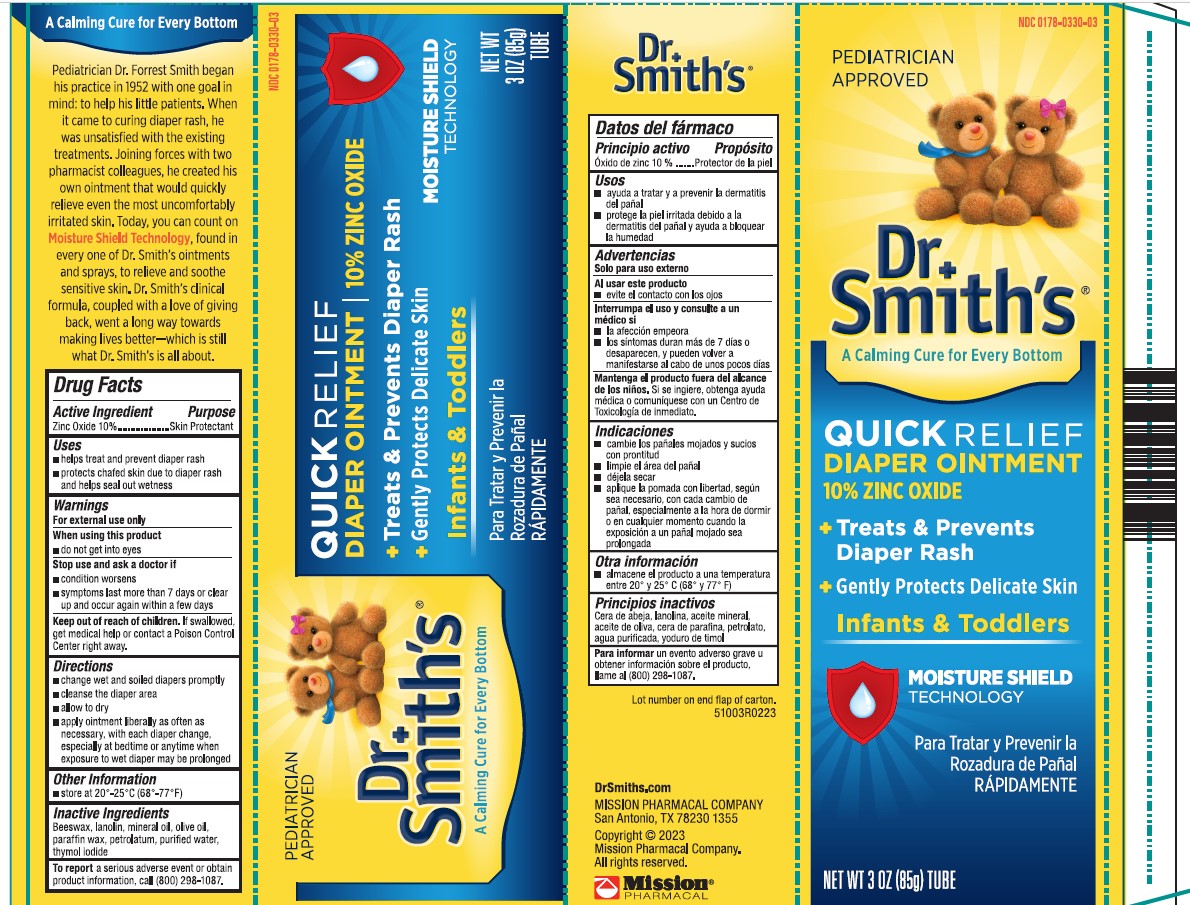 DRUG LABEL: DR SMITHS DIAPER
NDC: 0178-0330 | Form: OINTMENT
Manufacturer: Mission Pharmacal
Category: otc | Type: HUMAN OTC DRUG LABEL
Date: 20231005

ACTIVE INGREDIENTS: ZINC OXIDE 100 mg/1 g
INACTIVE INGREDIENTS: YELLOW WAX; LANOLIN; MINERAL OIL; OLIVE OIL; PARAFFIN; PETROLATUM; WATER; THYMOL IODIDE

Dr. Smith’s Diaper Rash Ointment

Active Ingredient

Zinc Oxide 10%

Purpose

Skin Protectant

Uses

- helps treat and prevent diaper rash
- protects chafed skin due to diaper rash and helps seal out wetness

Warnings

For external use only

When using this product,avoid contact with the eyes.

STOP USE

See a doctorif condition lasts more than 7 days.

KEEP OUT OF REACH OF CHILDREN

Keep this and all drugs out of the reach of children. If swallowed, get medical help or contact a Poison Control Center right away.

Directions

- change wet and soiled diapers promptly
- cleanse the diaper area
- allow to dry
- apply ointment liberally as often as necessary, with each diaper change, especially at bedtime or anytime when exposure to wet diapers may be prolonged.

Storage and Handling

Store between 15^0and 30^0C (59^0and 86^0F)

Inactive Ingredients

Beeswax, lanolin, mineral oil, olive oil, paraffin wax, petrolatum, purified water, thymol iodide

OTHER SAFETY INFORMATION

To reporta serious adverse event of obtain product information, call (201)-696-8400